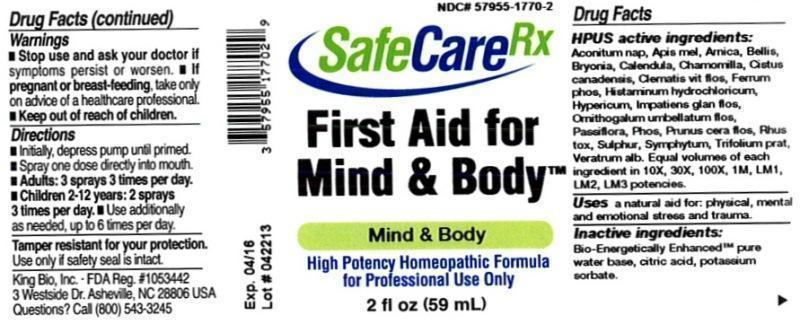 DRUG LABEL: First Aid for Mind and Body
NDC: 57955-1770 | Form: LIQUID
Manufacturer: King Bio Inc.
Category: homeopathic | Type: HUMAN OTC DRUG LABEL
Date: 20140401

ACTIVE INGREDIENTS: ACONITUM NAPELLUS 10 [hp_X]/59 mL; APIS MELLIFERA 10 [hp_X]/59 mL; ARNICA MONTANA 10 [hp_X]/59 mL; BELLIS PERENNIS 10 [hp_X]/59 mL; BRYONIA ALBA ROOT 10 [hp_X]/59 mL; CALENDULA OFFICINALIS FLOWERING TOP 10 [hp_X]/59 mL; MATRICARIA RECUTITA 10 [hp_X]/59 mL; HELIANTHEMUM CANADENSE 10 [hp_X]/59 mL; CLEMATIS VITALBA FLOWER 10 [hp_X]/59 mL; FERROSOFERRIC PHOSPHATE 10 [hp_X]/59 mL; HISTAMINE DIHYDROCHLORIDE 10 [hp_X]/59 mL; HYPERICUM PERFORATUM 10 [hp_X]/59 mL; IMPATIENS GLANDULIFERA FLOWER 10 [hp_X]/59 mL; ORNITHOGALUM UMBELLATUM FLOWERING TOP 10 [hp_X]/59 mL; PASSIFLORA INCARNATA FLOWERING TOP 10 [hp_X]/59 mL; PHOSPHORUS 10 [hp_X]/59 mL; PRUNUS CERASIFERA FLOWER 10 [hp_X]/59 mL; TOXICODENDRON PUBESCENS LEAF 10 [hp_X]/59 mL; SULFUR 10 [hp_X]/59 mL; COMFREY ROOT 10 [hp_X]/59 mL; TRIFOLIUM PRATENSE FLOWER 10 [hp_X]/59 mL; VERATRUM ALBUM ROOT 10 [hp_X]/59 mL
INACTIVE INGREDIENTS: WATER; CITRIC ACID MONOHYDRATE; POTASSIUM SORBATE

ACTIVE INGREDIENT

Drug Facts__________________________________________________________________________________________________________

HPUS activeingredients: Aconitum napellus, Apis mellifica, Arnica montana, Bellis perennis, Bryonia, Calendula officinalis, Chamomilla, Cistus canadensis, Clematis vitalba, flos, Ferrum phosphoricum, Histaminum hydrochloricum, Hypericum perforatum, Impatiens glandulifera, flos, ornithogalum umbellatum, flos, Passiflora incarnata, Phosphorus, Prunus cerasifera, flos, Rhus toxicodendron, sulphur, Symphytum officinale, Trifolium pratense, Veratrum album. Equal volumes of each ingredient in 10X, 30X, 100X, 1M, LM1, LM2, LM3 potencies.

INDICATIONS AND USAGE

Uses a natural aid for: physical, mental and emotional stress and trauma.

Inactive Ingredients:

Bio-Energetically Enhanced™ pure water, citric acid and potassium sorbate.

Warnings

- Stop use and ask your doctor if symptoms persist or worsen.
- If pregnant or breast-feeding, take only on advice of a healthcare professional.

- Keep out of reach of children

Directions

- Initially, depress pump until primed.
- Spray one dose directly into mouth.
- Adults: 3 sprays 3 times per day.
- Children 2-12 years: 2 sprays 3 times per day.
- Use additonally as needed, up to 6 times per day.

OTHER SAFETY INFORMATION

Tamper resistant for your protection. Use only if safety seal is intact.

PURPOSE

Uses a natural aid for:

- physical, mental and emotional stress and trauma.